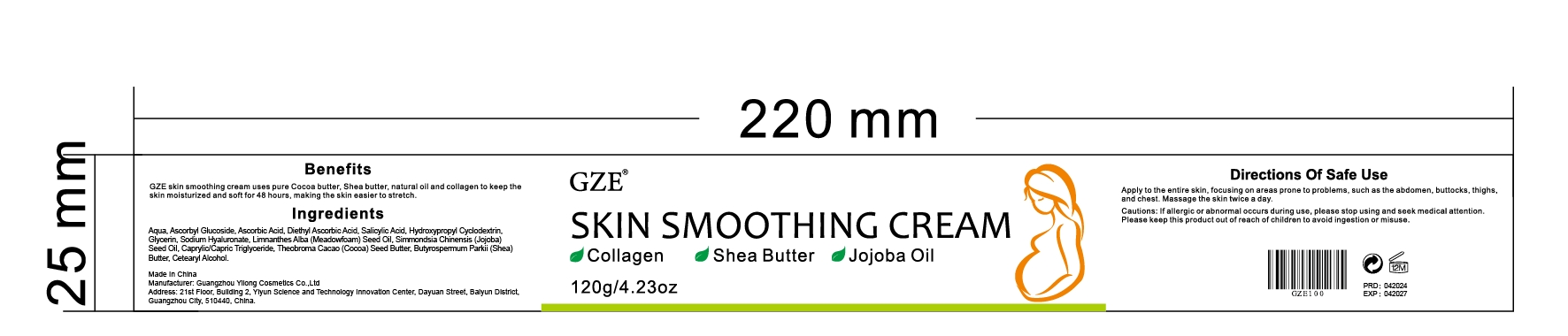 DRUG LABEL: GZE Skin Smoothing Cream
NDC: 83566-105 | Form: CREAM
Manufacturer: Guangdong Aimu Biological Technology Co., Ltd.
Category: otc | Type: HUMAN OTC DRUG LABEL
Date: 20240515

ACTIVE INGREDIENTS: SALICYLIC ACID 1 g/120 g
INACTIVE INGREDIENTS: COCOA BUTTER; BUTYROSPERMUM PARKII (SHEA) BUTTER UNSAPONIFIABLES; WATER; ASCORBIC ACID; JOJOBA OIL; CAPRYLIC/CAPRIC MONO/DI-GLYCERIDES; ASCORBYL GLUCOSIDE; MEADOWFOAM SEED OIL; GLYCERIN; PEG-9 DIGLYCIDYL ETHER/SODIUM HYALURONATE CROSSPOLYMER

GZE Skin Smoothing Cream

Active ingredients

SALICYLIC ACID 1%

Purpose

Moisturising.

Uses

Apply to the entire skin, focusing on areas prone to problems, such as the abdomen, buttocks, thighs and chest.Massage the skin twice a day.

WARNINGS

For external use only.

Stop use and ask a doctor if

rash occurs.

Do not use

on damaged or broken skin.

When using this product

keep out of eyes. Rinse with water to remove.

Keep out of reach of children.

If swallowed, get medical help or contact a Poison Control Center right away.

INACTIVE INGREDIENT

COCOA BUTTER
BUTYROSPERMUM PARKII (SHEA) BUTTER UNSAPONIFIABLES
WATER
ASCORBIC ACID
JOJOBA OIL
CAPRYLIC/CAPRIC MONO/DI-GLYCERIDES
ASCORBYL GLUCOSIDE
MEADOWFOAM SEED OIL
GLYCERIN
PEG-9 DIGLYCIDYL ETHERISODIUM HYALURONATE CROSSPOLYMER